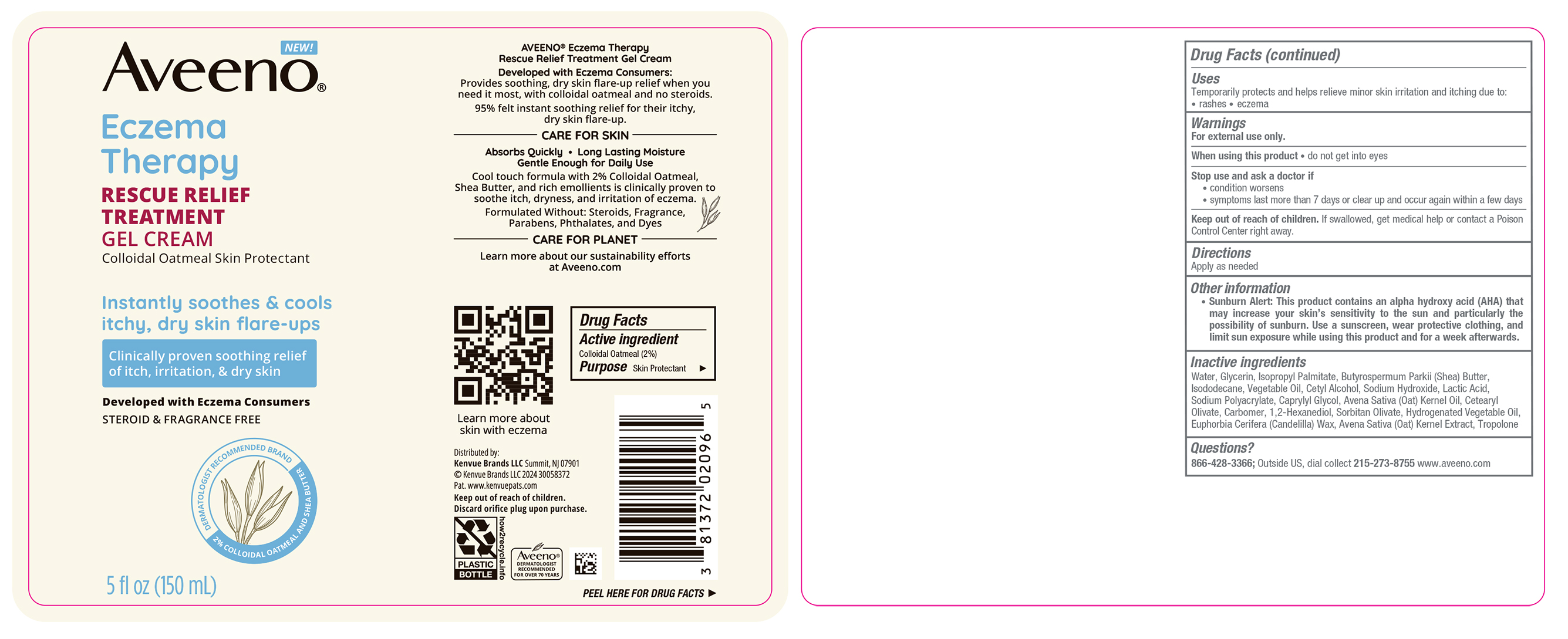 DRUG LABEL: Aveeno Eczema Therapy Rescue Relief Treatment
NDC: 69968-0802 | Form: CREAM
Manufacturer: Kenvue Brands LLC
Category: otc | Type: HUMAN OTC DRUG LABEL
Date: 20241206

ACTIVE INGREDIENTS: OATMEAL 20 mg/1 mL
INACTIVE INGREDIENTS: TROPOLONE; OAT KERNEL OIL; SHEA BUTTER; CETYL ALCOHOL; CAPRYLYL GLYCOL; CETEARYL OLIVATE; CARBOMER HOMOPOLYMER, UNSPECIFIED TYPE; 1,2-HEXANEDIOL; SORBITAN OLIVATE; WATER; GLYCERIN; ISOPROPYL PALMITATE; ISODODECANE; SODIUM HYDROXIDE; LACTIC ACID; CANDELILLA WAX; OAT

Aveeno Eczema Therapy Rescue Relief Treatment Gel Cream

Drug Facts

Active Ingredient

Colloidal Oatmeal 2%

Purpose

Skin Protectant

Uses

- Temporarily protects and helps relieve minor skin irritation and itching due to: • rashes • eczema

Warnings

For external use only.

When using this product

- Do not get into eyes

Stop use and ask a doctor if

- condition worsens
- symptoms last more than 7 days or clear up and occur again within a few days

Keep out of reach of children. If swallowed, get medical help or contact a Poison Control Center right away.

Directions

Apply as needed

Other Information

- Sunburn Alert: This product contains an alpha hydroxy acid (AHA) that may increase your skin’s sensitivity to the sun and particularly the possibility of sunburn. Use a sunscreen, wear protective clothing, and limit sun exposure while using this product and for a week afterwards.

Inactive Ingredients

Water, Glycerin, Isopropyl Palmitate, Butyrospermum Parkii (Shea) Butter, Isododecane, Vegetable Oil, Cetyl Alcohol, Sodium Hydroxide, Lactic Acid, Sodium Polyacrylate, Caprylyl Glycol, Avena Sativa (Oat) Kernel Oil, Cetearyl Olivate, Carbomer, 1,2-Hexanediol, Sorbitan Olivate, Hydrogenated Vegetable Oil, Euphorbia Cerifera (Candelilla) Wax, Avena Sativa (Oat) Kernel Extract, Tropolone

Questions?

866-428-3366; Outside US, dial collect 215-273-8755 www.aveeno.com

Distributed by:
Kenvue Brands LLC
Summit, NJ 07901

PRINCIPAL DISPLAY PANEL - 150mL Bottle Label

NEW!

Aveeno®

Eczema

Therapy

RESCUE RELIEF

TREATMENT

GEL CREAM

Colloidal Oatmeal Skin Protectant

Instantly soothes & cools

itchy, dry skin flare-ups

Clinically proven soothing relief

of itch, irritation, & dry skin

Developed with Eczema Consumers

STEROID & FRAGRANCE FREE

DERMATOLOGIST RECOMMENDED BRAND

2% COLLOIDAL OATMEAL AND SHEA BUTTER

5 fl oz (150mL)